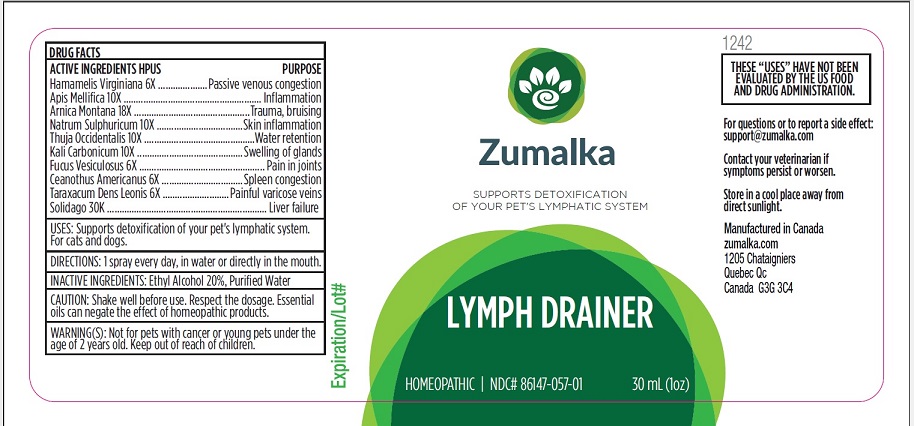 DRUG LABEL: LYMPH DRAINER
NDC: 86147-057 | Form: LIQUID
Manufacturer: Groupe Cyrenne Inc.
Category: homeopathic | Type: OTC ANIMAL DRUG LABEL
Date: 20251120

ACTIVE INGREDIENTS: HAMAMELIS VIRGINIANA LEAF 6 [hp_X]/30 mL; APIS MELLIFERA 10 [hp_X]/30 mL; THUJA OCCIDENTALIS LEAFY TWIG 10 [hp_X]/30 mL; SODIUM SULFIDE NONAHYDRATE 10 [hp_X]/30 mL; CEANOTHUS AMERICANUS LEAF 6 [hp_X]/30 mL; ARNICA MONTANA FLOWER 18 [hp_X]/30 mL; POTASSIUM CARBONATE 10 [hp_X]/30 mL; TARAXACUM PALUSTRE ROOT 6 [hp_X]/30 mL; SOLIDAGO VIRGAUREA FLOWERING TOP 30 [hp_X]/30 mL; FUCUS VESICULOSUS 6 [hp_X]/30 mL
INACTIVE INGREDIENTS: ALCOHOL; WATER

Active ingredients Purpose

Hamamelis Virginiana 6x Passive venous congestion

Apis Mellifica 10x Inflammation

Natrum Sulphuricum 10x Skin inflammation

Thuja Occidentalis 10x Water retention

Arnica Montana 18x Trauma, bruising

Kali Carbonicum 10x Swelling of glands

Fucus Vesiculosus 6x Pain in joints

Ceanothus Americanus 6x Spleen congestion

Taraxacum Dens Leonis 6x Painful varicose veins

Solidago 30k Liver failure

Uses

Naturally detoxifies your pet's lymphatic system. For cats and dogs only.

Warnings

Keep out of reach of children.Not for pets with cancer or young pets under the age of 2 years old.

Direction

1 spray every day, in water or directly in the mouth.

Inactive ingredients

Ethyl alcohol 20%, purified water

Cautions

Shake well before use. Respect the dosage. Essential oils can negate the effects of homeopathic products. Store in a cool place away from direct sunlight.